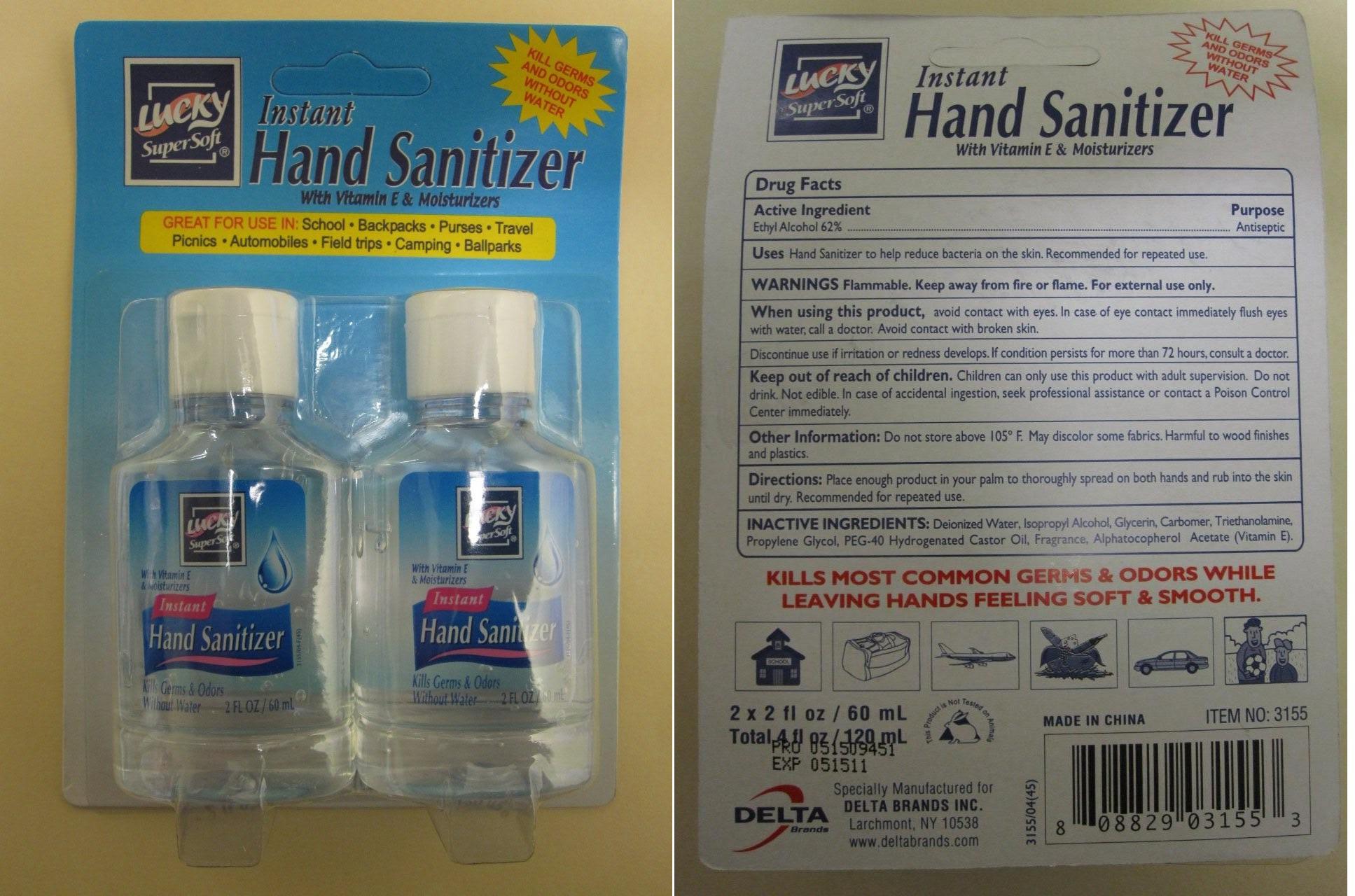 DRUG LABEL: Lucky Instant Hand Cleanser with Vitamin E
NDC: 20276-155 | Form: LIQUID
Manufacturer: Delta Brands Inc
Category: otc | Type: HUMAN OTC DRUG LABEL
Date: 20091208

ACTIVE INGREDIENTS: ALCOHOL 62 mL/100 mL
INACTIVE INGREDIENTS: WATER; ISOPROPYL ALCOHOL; GLYCERIN; TROLAMINE; PROPYLENE GLYCOL; POLYOXYL 40 HYDROGENATED CASTOR OIL; ALPHA-TOCOPHEROL ACETATE

Drug Facts

Active Ingredient

Ethyl Alcohol 62%

Purpose

Antiseptic

Uses

Hand Sanitizer to help reduce bacteria on the skin. Recommended for repeated use.

Warnings

Flammable. Keep away from fire and flame. For external use only

When using this product

avoid contact with eyes an mucous membranes. In case of eye contact; immediately flush eyes with water, call a doctor. Avoid contact with broken skin.
Discontinue use if irritation develops. If condition persists for more than 72 hours, consult a doctor.

Keep out of reach of children

Children can only use this product with adult supervision. Do not drink. Not edible. In case of accidental ingestion seek professional assistance or Poison Control Center immediately.

Other Information

Do not store above 105F. May discolor some fabrics. Harmful to wood finishes and plastics

Directions

Place enough product in your palm to thoroughly spread on both hands and rub into the skin until dry. Recommended for repeated use

INACTIVE INGREDIENT

Deionized Water, Isopropyl Alcohol, Glycerin, Carbomer, Triethanolamine, Propylene Glycol, PEG-40 Hydrogenated Castor Oil, Fragrance, Alphatocopherol Acetate (Vitamin E)

Package Label